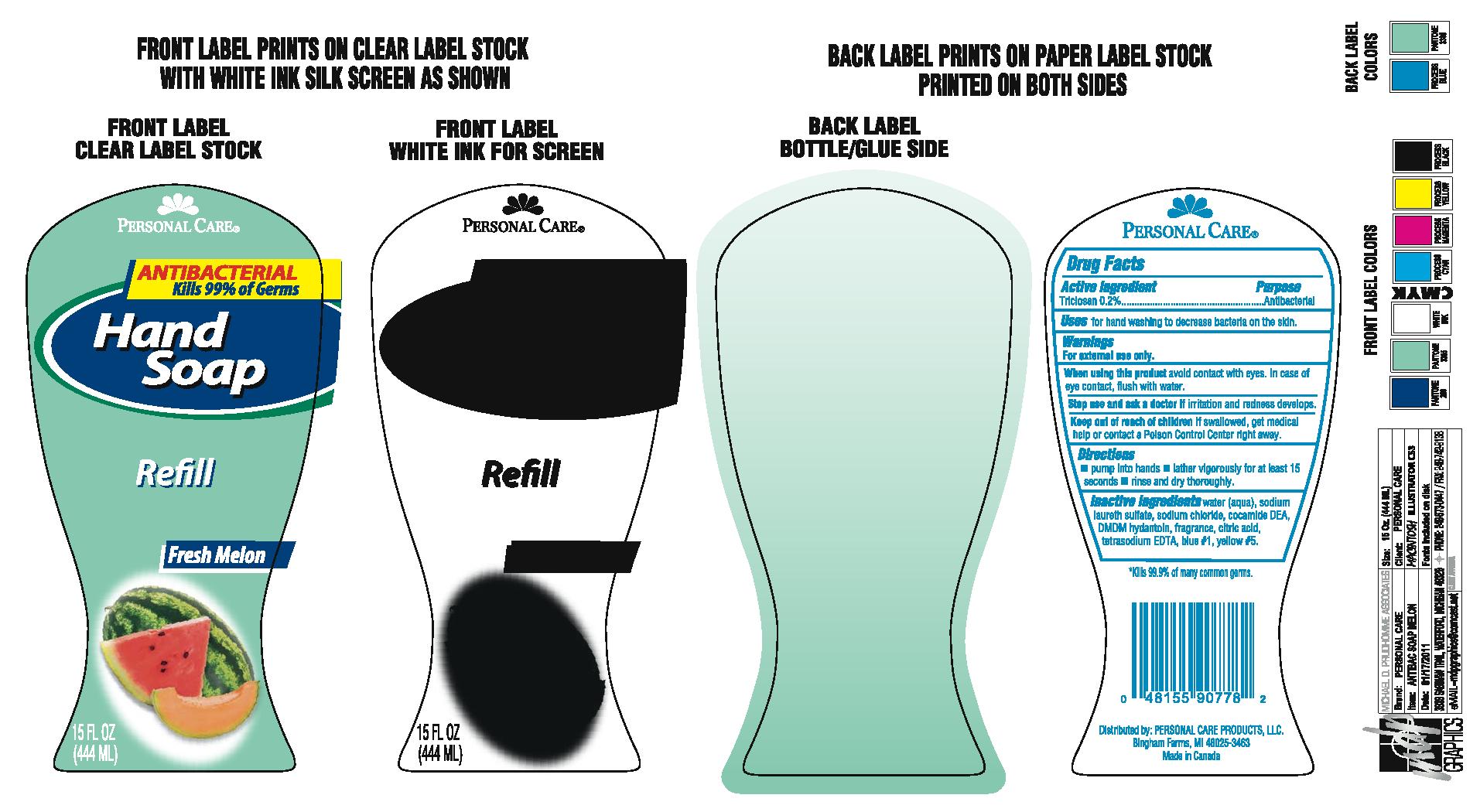 DRUG LABEL: hand
NDC: 29500-907 | Form: SOAP
Manufacturer: Personal Care Products
Category: otc | Type: HUMAN OTC DRUG LABEL
Date: 20111108

ACTIVE INGREDIENTS: TRICLOSAN .888 mL/444 mL
INACTIVE INGREDIENTS: WATER; SODIUM LAURETH SULFATE; SODIUM CHLORIDE; COCO DIETHANOLAMIDE; DMDM HYDANTOIN; CITRIC ACID MONOHYDRATE; EDETATE SODIUM; FD&C BLUE NO. 1; FD&C YELLOW NO. 5

Hand Melon

Active Ingredient

Triclosan 0.2%

Purpose

Antibacterial

Keep out of reach of children If swallowed get medical help or contact a poison control center right away.

INDICATIONS AND USAGE

Uses for hand washing to decrease bacteria on the skin

Warnings

For external use only

When using this product avoid contact with eyes.In case of eye contact flush with water.

Stop use and ask a doctor if irritation and redness develops

Directions

pump into hands

lather vigorously for at least 15 seconds

rinse and dry thoroughly

Inactive ingredients

water (aqua), sodium laureth sulfate, sodium chloride, cocamide DEA, DMDM hydantoin, fratetrasodium EDTA, fragrance, citric acid, blue #1, yellow #5

PACKAGE LABEL

Personal Care

Antibacterial Kills 99% of germs

Hand soap

Fresh Melon Refill

15 fl oz (444ml)